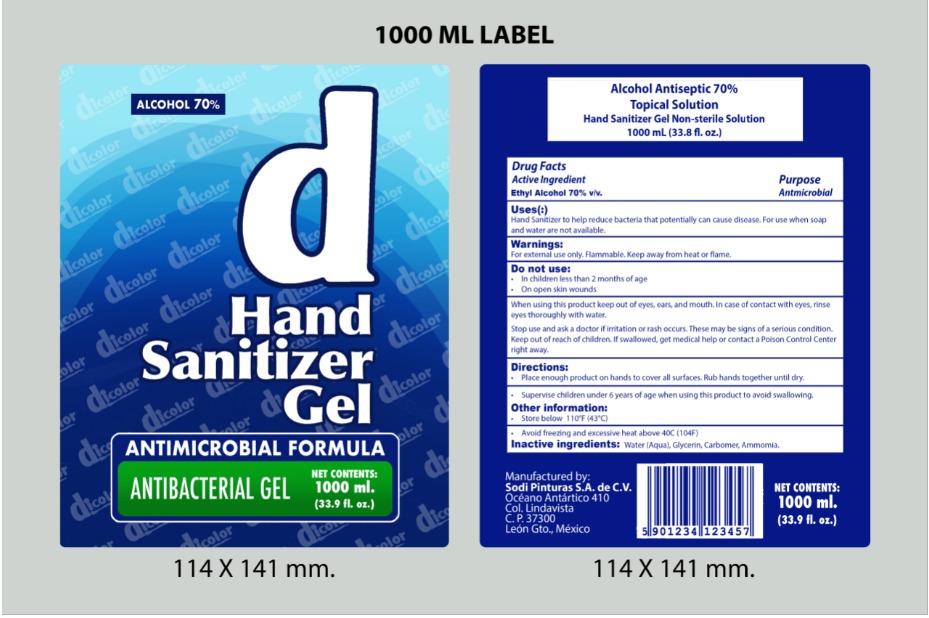 DRUG LABEL: dicolor
NDC: 79050-0040 | Form: GEL
Manufacturer: SODI PINTURAS, S.A. DE C.V.
Category: otc | Type: HUMAN OTC DRUG LABEL
Date: 20201104

ACTIVE INGREDIENTS: ALCOHOL 0.7 mL/1 mL
INACTIVE INGREDIENTS: WATER 0.248 mL/1 mL; AMMONIA 0.007 mL/1 mL; GLYCERIN 0.02 mL/1 mL; CARBOMER 940 0.025 mL/1 mL

dicolor Hand Sanitizer Gel

DIRECTIONS DOSAGE AND ADMINISTRATION

Directions

Place enough product on hands to cover all surfaces. Rub hands together until dry.

INACTIVE INGREDIENTS

Inactive ingredients Water (Aqua), Glycerin, Carbomer, Triethanolamine

INDICATIONS AND USAGE

Use[s]

Hand Sanitizer to help reduce bacteria that potentially can cause disease. For use when soap and water are not available.

Keep out of reach of children. If swallowed, get medical help or contact a Poison Control Center right away.

PURPOSE

Purpose Antmicrobial

WARNINGS AND PRECAUTIONS

Store below 110°F (43°C)

Avoid freezing and excessive heat above 40C (104F)

Supervise children under 6 years of age when using this product to avoid swallowing.

When using this product keep out of eyes, ears, and mouth. In case of contact with eyes, rinse eyes thoroughly with water.

WARNINGS

For external use only. Flammable. Keep away from heat or flame

ACTIVE INGREDIENT

Active ingredient Ethyl Alcohol 70% v/v

ASK A DOCTOR

Stop use and ask a doctor if irritation or rash occurs. These may be signs of a serious condition.

STOP USE

Stop use and ask a doctor if irritation or rash occurs. These may be signs of a serious condition.